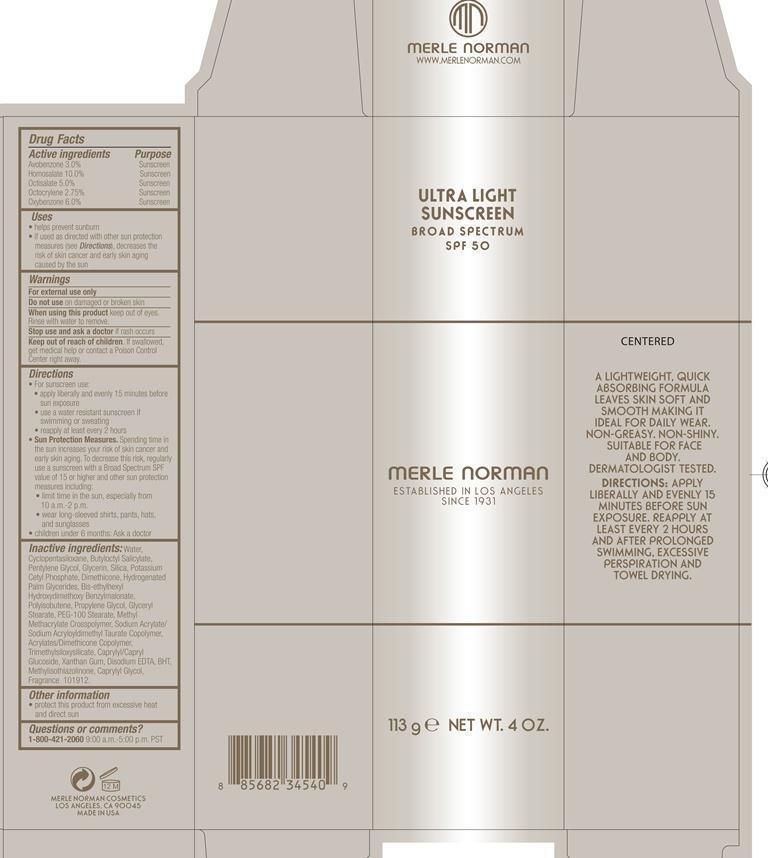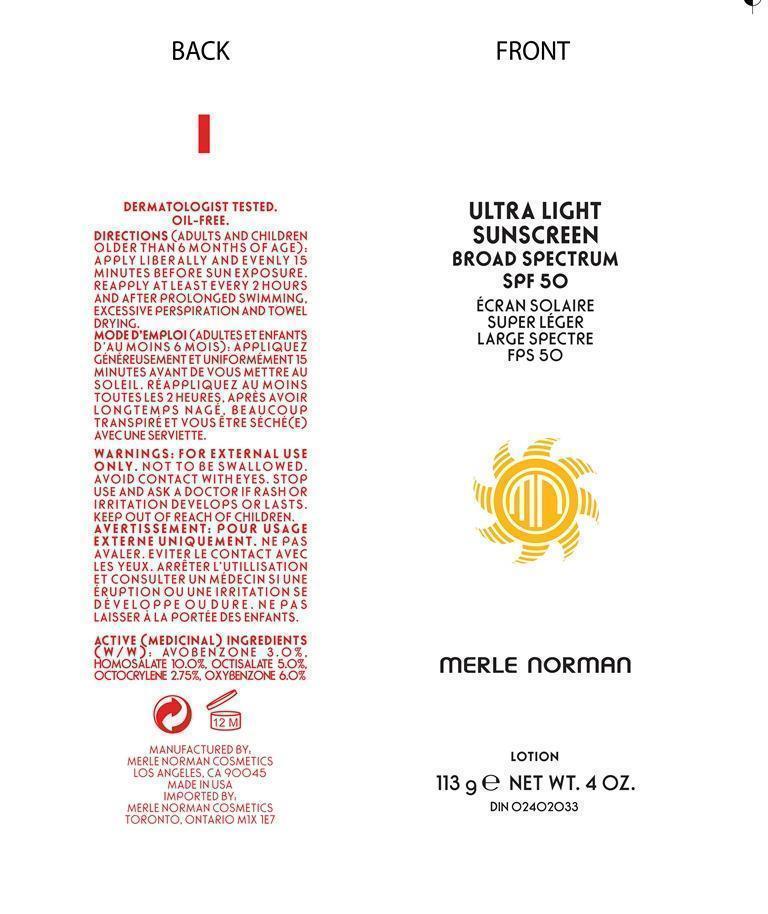 DRUG LABEL: Ultra Light Sunscreen Broad Spectrum SPF 50
NDC: 57627-117 | Form: LOTION
Manufacturer: Merle Norman Cosmetics
Category: otc | Type: HUMAN OTC DRUG LABEL
Date: 20200127

ACTIVE INGREDIENTS: AVOBENZONE 3.39 g/113 g; HOMOSALATE 11.3 g/113 g; OCTISALATE 5.65 g/113 g; OCTOCRYLENE 3.11 g/113 g; OXYBENZONE 6.78 g/113 g
INACTIVE INGREDIENTS: WATER; CYCLOMETHICONE 5; BUTYLOCTYL SALICYLATE; PENTYLENE GLYCOL; GLYCERIN; SILICON DIOXIDE; POTASSIUM CETYL PHOSPHATE; DIMETHICONE; BIS-ETHYLHEXYL HYDROXYDIMETHOXY BENZYLMALONATE; POLYISOBUTYLENE (1000 MW); PROPYLENE GLYCOL; GLYCERYL MONOSTEARATE; PEG-100 STEARATE; SODIUM ACRYLATE/SODIUM ACRYLOYLDIMETHYLTAURATE COPOLYMER (4000000 MW); CAPRYLYL/CAPRYL OLIGOGLUCOSIDE; XANTHAN GUM; EDETATE DISODIUM; BUTYLATED HYDROXYTOLUENE; METHYLISOTHIAZOLINONE; CAPRYLYL GLYCOL

Ultra Light Sunscreen Broad Spectrum SPF 50

Active ingredients Purpose

Avobenzone 3.0% Sunscreen

Homosalate 10.0% Sunscreen

Octisalate 5.0% Sunscreen

Octocrylene 2.75% Sunscreen

Oxybenzone 6.0% Sunscreen

Uses
· helps prevent sunburn
· If used as directed with other sun protection measures (see Directions),
decreases the risk of skin cancer and early skin aging caused by the sun

Keep out of reach of children. If swallowed, get medical help or contact a Poison Control Center right away.

Stop use and ask a doctor if rash occurs

Warnings

For external use only

Do not use on damaged or broken skin

When using this product keep out of eyes. Rinse with water to remove.

Directions

• For sunscreen use:

• apply liberally and evenly 15 minutes before sun exposure

• use a water resistant sunscreen if swimming or sweating

• reapply at least every 2 hours

Sun Protection Measures. Spending time in the sun increases your risk of skin cancer and early skin aging. To decrease this risk, regularly

use a sunscreen with a Broad Spectrum SPF value of 15 or higher and other sun protection measures including:

• limit time in the sun, especially from 10 a.m.-2 p.m.

• wear long-sleeved shirts, pants, hats, and sunglasses

• children under 6 months: Ask a doctor

Inactive ingredients:

Water, Cyclopentasiloxane, Butyloctyl Salicylate, Pentylene Glycol, Glycerin, Silica, Potassium Cetyl Phosphate, Dimethicone, Hydrogenated Palm Glycerides, Bis-ethylhexyl Hydroxydimethoxy Benzylmalonate, Polyisobutene, Propylene Glycol, Glyceryl Stearate, PEG-100 Stearate, Methyl Methacrylate Crosspolymer, Sodium Acrylate/ Sodium Acryloyldimethyl Taurate Copolymer, Acrylates/Dimethicone Copolymer, Trimethylsiloxysilicate, Caprylyl/Capryl Glucoside, Xanthan Gum, Disodium EDTA, BHT, Methylisothiazolinone, Caprylyl Glycol, Fragrance

PACKAGE LABEL

ULTRA LIGHT SUNSCREEN

BROAD SPECTRUM SPF 50

Merle Norman

Established in Los Angeles since 1931

113 g NET WT. 4 OZ.